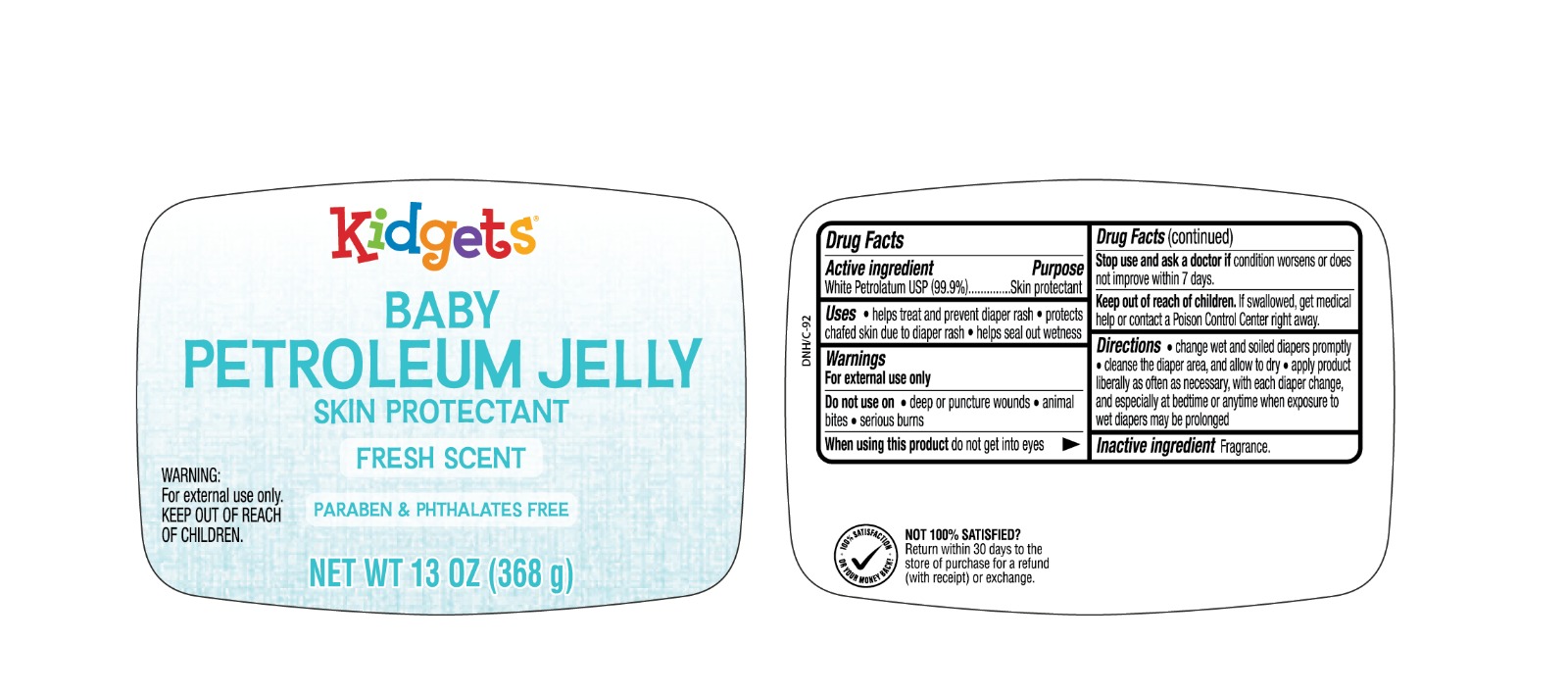 DRUG LABEL: Kidgets Baby Petroleum Jelly
NDC: 51628-4250 | Form: JELLY
Manufacturer: MY IMPORTS USA LLC
Category: otc | Type: HUMAN OTC DRUG LABEL
Date: 20250824

ACTIVE INGREDIENTS: PETROLATUM 99.9 g/100 g
INACTIVE INGREDIENTS: FRAGRANCE 13576 0.01 g/100 g

Kidgets Baby Petroleum Jelly

Active Ingredient

White Petrolatum USP (99.9%)

Inactive Ingredients

Fragrance

Purpose

Skin Protectant

Uses

temporarily protects minor: cuts, scrapes, burns; temporarily protects and helps relieve chapped or cracked skin and lips; helps protect from the drying effects of wind and cold weather

Warnings

For external use only

When using this product

do not get into eyes

See a doctor if

condition lasts more than 7 days

Do not use on

deep or puncture wounds, animal bites, serious burns

Keep out of reach of children.

If swallowed, get medical help or contact a Poison Control Center right away.

Directions

change wet and soiled diapers promptly. Cleanse the diaper area and allow to dry. Apply liberally as often as required with each diaper change and especially at bedtime or anytime when exposure to wet diaper may be prolonged.